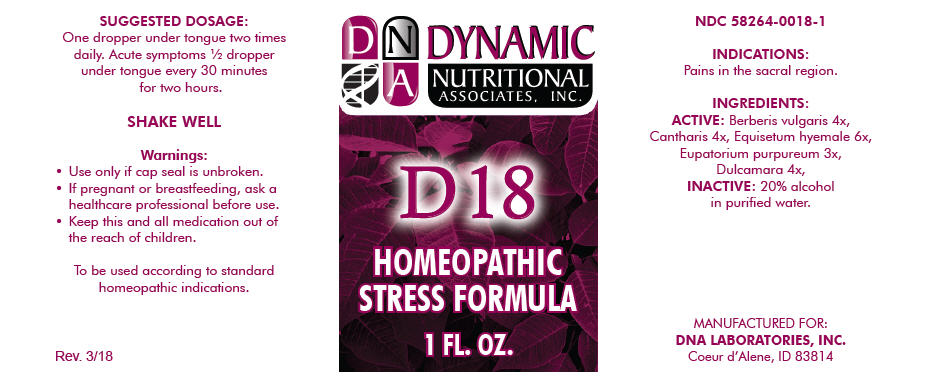 DRUG LABEL: D-18
NDC: 58264-0018 | Form: SOLUTION/ DROPS
Manufacturer: DNA Labs, Inc.
Category: homeopathic | Type: HUMAN OTC DRUG LABEL
Date: 20250113

ACTIVE INGREDIENTS: BERBERIS VULGARIS ROOT BARK 4 [hp_X]/1 mL; LYTTA VESICATORIA 4 [hp_X]/1 mL; EQUISETUM HYEMALE 6 [hp_X]/1 mL; EUTROCHIUM PURPUREUM ROOT 3 [hp_X]/1 mL; SOLANUM DULCAMARA STEM 4 [hp_X]/1 mL
INACTIVE INGREDIENTS: ALCOHOL; WATER

D-18

NDC 58264-0018-1

INDICATIONS

PURPOSE

Pains in the sacral region.

INGREDIENTS

ACTIVE

Berberis vulgaris 4x, Cantharis 4x, Equisetum hyemale 6x, Eupatorium purpureum 3x, Dulcamara 4x,

INACTIVE

20% alcohol in purified water.

SUGGESTED DOSAGE

One dropper under tongue two times daily. Acute symptoms ½ dropper under tongue every 30 minutes for two hours.

STORAGE AND HANDLING

SHAKE WELL

Warnings

- Use only if cap seal is unbroken.

PREGNANCY OR BREAST FEEDING

- If pregnant or breastfeeding, ask a healthcare professional before use.

KEEP OUT OF REACH OF CHILDREN

- Keep this and all medication out of the reach of children.

To be used according to standard homeopathic indications.

PRINCIPAL DISPLAY PANEL - 1 FL. OZ. Bottle Label

DYNAMIC
NUTRITIONAL
ASSOCIATES, INC.

D 18

HOMEOPATHIC
STRESS FORMULA

1 FL. OZ.